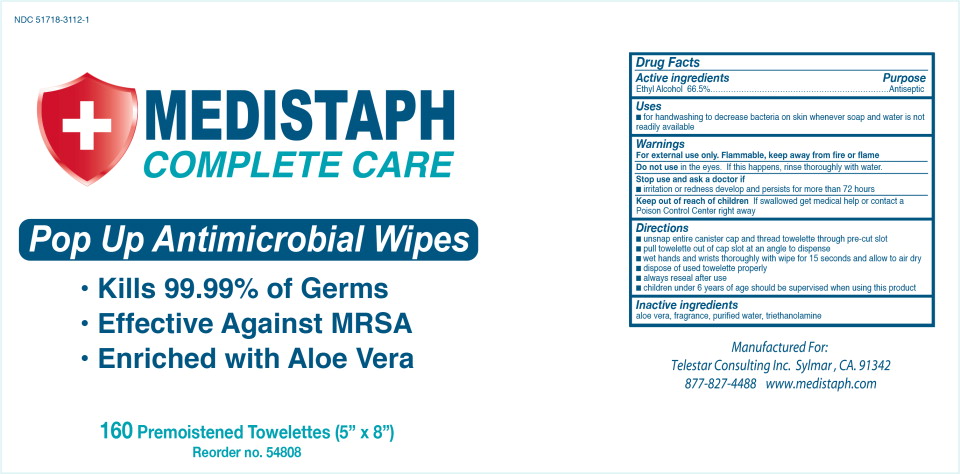 DRUG LABEL: Antiseptic
NDC: 51718-3112 | Form: LIQUID
Manufacturer: Telestar 
Category: otc | Type: HUMAN OTC DRUG LABEL
Date: 20150319

ACTIVE INGREDIENTS: alcohol 665 mL/1 L
INACTIVE INGREDIENTS: aloe vera leaf; water; trolamine

Drug Facts

Active ingredients

Ethyl Alcohol 66.5%

Purpose

Antiseptic

Uses

- for handwashing to decrease bacteria on skin whenever soap and water is not readily available

Warnings

For external use only. Flammable, keep away from fire or flame

Do not use in the eyes. If this happens, rinse thoroughly with water.

Stop use and ask a doctor if

- irritation or redness develop and persists for more than 72 hours

Keep out of reach of children If swallowed get medical help or contact a Poison Control Center right away

Directions

- unsnap entire canister cap and thread towelette through pre-cut slot
- pull towelette out of cap slot at an angle to dispense
- wet hands and wrists thoroughly with wipe for 15 seconds and allow to air dry
- dispose of used towelette properly
- always reseal after use
- children under 6 years of age should be supervised when using this product

Inactive ingredients

aloe vera, fragrance, purified water, triethanolamine

Principal Display Panel - Canister Label

NDC 51718-3112-1

MEDISTAPH
COMPLETE CARE

Pop Up Antimicrobial Wipes

- Kills 99.99% of Germs
- Effective Against MRSA
- Enriched with Aloe Vera

160 Premoistened Towlettes (5" x 8")

Reorder no. 54808